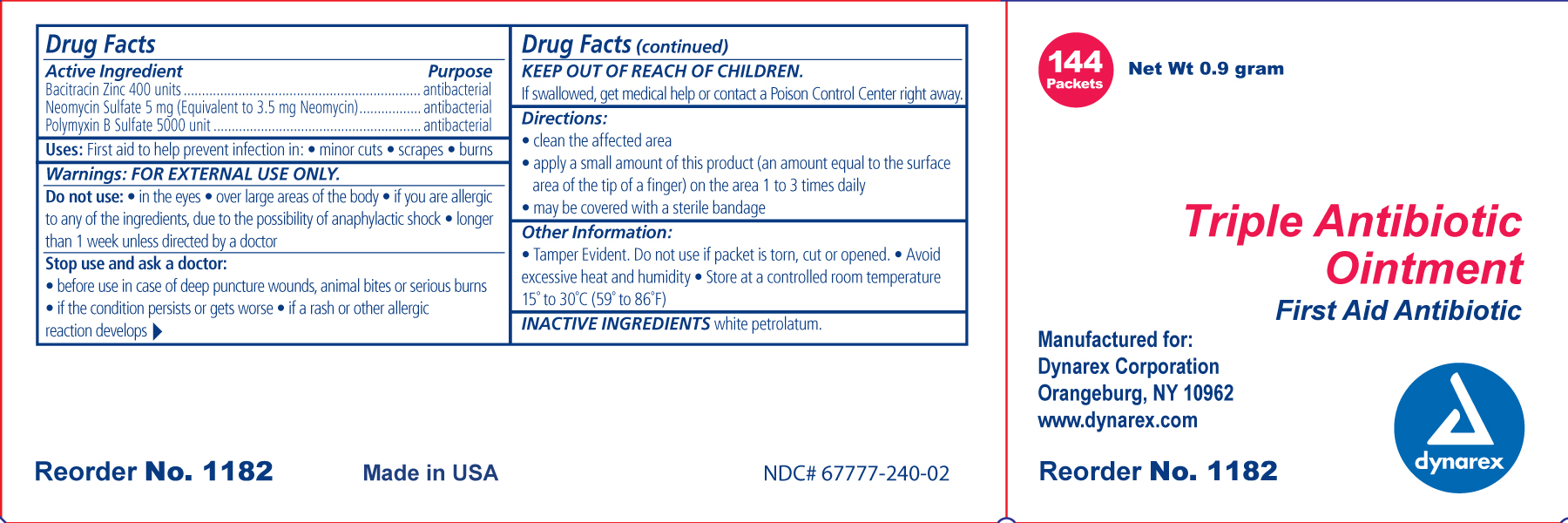 DRUG LABEL: bacitracin zinc, neomycin sulfate and polymyxin b sulfate
NDC: 67777-240 | Form: OINTMENT
Manufacturer: Dynarex Corporation
Category: otc | Type: HUMAN OTC DRUG LABEL
Date: 20110323

ACTIVE INGREDIENTS: BACITRACIN ZINC 400 [iU]/1 g; NEOMYCIN SULFATE 3.5 mg/1 g; POLYMYXIN B SULFATE 5000 [iU]/1 g
INACTIVE INGREDIENTS: PETROLATUM

Triple Antibiotic

Active ingredient (in ea. gram) Purpose
Bacitracin Zinc 400 Units antibacterial

Neomyxin Sulfate 5mg (Equivalent to 3.5 mg Neomyxin) antibacterial

Polymyxin B Sulfate 5000 Units antibacterial

Uses triple antibiotic :

First aid to help prevent infection in:

- Minor cuts
- scrapes
- burns

Ask a doctor before use:

- in case of deep or puncture wounds
- animal bites
- serious burns

Other information

- store at controlled room temperature 15°-30° C (59°-86° F)
- avoid excessive heat and humidity
- Tamper Evident. Do not use if packet is torn, cut or open.

Inactive ingredients:

White petrolatum

Directions triple antibiotic:

- clean affected areas
- apply a small amount of product (an amount equal to the surface area of the tip of the finger) on the area 1 to 3 times daily
- may be covered with a sterile bandage

KEEP OUT OF REACH OF CHILDREN If swallowed, get medical help or contact a Poison Control Center right away.

INDICATIONS AND USAGE

First aid antibacterial ointment to help prevent infection in minor cuts, scrapes and burns.

Warnings

For external use only

Principal Display Panel

Triple Antibiotic